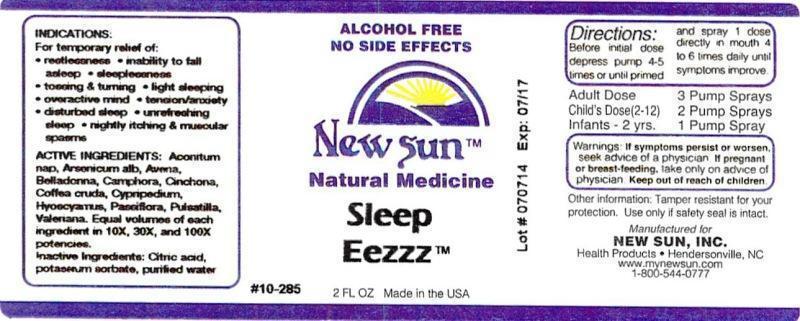 DRUG LABEL: Sleep Eezzz
NDC: 66579-0009 | Form: LIQUID
Manufacturer: New Sun Inc.
Category: homeopathic | Type: HUMAN OTC DRUG LABEL
Date: 20140730

ACTIVE INGREDIENTS: ACONITUM NAPELLUS 10 [hp_X]/59 mL; ARSENIC TRIOXIDE 10 [hp_X]/59 mL; AVENA SATIVA FLOWERING TOP 10 [hp_X]/59 mL; ATROPA BELLADONNA 10 [hp_X]/59 mL; CAMPHOR (NATURAL) 10 [hp_X]/59 mL; CINCHONA OFFICINALIS BARK 10 [hp_X]/59 mL; ARABICA COFFEE BEAN 10 [hp_X]/59 mL; CYPRIPEDIUM PARVIFOLUM ROOT 10 [hp_X]/59 mL; HYOSCYAMUS NIGER 10 [hp_X]/59 mL; PASSIFLORA INCARNATA FLOWERING TOP 10 [hp_X]/59 mL; PULSATILLA VULGARIS 10 [hp_X]/59 mL; VALERIAN 10 [hp_X]/59 mL
INACTIVE INGREDIENTS: CITRIC ACID MONOHYDRATE; POTASSIUM SORBATE; WATER

Sleep Eezzz

DOSAGE AND ADMINISTRATION

Directions: Before initial dose depress pump 4-5 times or until primed and spray 1 dose directly in mouth 4 to 6 times daily until symptoms improve.

Adult Dose: 3 Pump Sprays

Child's Dose: (2-12): 2 Pump Sprays

Infants-2 yrs: 1 Pump Spray

WARNINGS

Warnings: If symptoms persist or worsen, seek advice of physician. If pregnant or breast-feeding, take only on advice of physician.

Keep out of reach of children.

Other information: Tamper resistant for your protection. Use only if safety seal is intact.

PURPOSE

Indications: For temporary relief of: •restlessness •inability to fall asleep •sleeplessness •tossing & turning •light sleeping •overactive mind •tension/anxiety •disturbed sleep •unrefreshing sleep •nightly itching & muscular spasms

ACTIVE INGREDIENT

Active Ingredients: Aconitum napellus, Arsenicum album, Avena sativa, Belladonna, Camphora, Cinchona officinalis, Coffea cruda, Cypripedium pubescens, Hyoscyamus niger, Passiflora incarnata, Pulsatilla, Valeriana officinalis. Equal volumes of each ingredient in 10X, 30X, and 100X potencies.

Inactive Ingredient: Citric acid, potassium sorbate, purified water.

INDICATIONS AND USAGE

Indications: For temporary relief of: restlessness •inability to fall asleep •sleeplessness •tossing & turning •light sleeping •overactive mind •tension/anxiety •disturbed sleep •unrefreshing sleep •nightly itching & muscular spasms